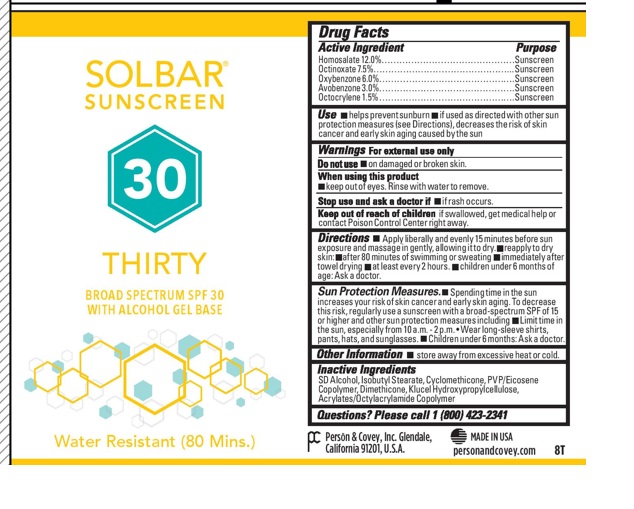 DRUG LABEL: Solbar Thirty SPF 30
NDC: 0096-0685 | Form: CREAM
Manufacturer: Person and Covey
Category: otc | Type: HUMAN OTC DRUG LABEL
Date: 20251204

ACTIVE INGREDIENTS: HOMOSALATE 0.12 g/1 g; OCTINOXATE 0.075 g/1 g; OXYBENZONE 0.06 g/1 g; AVOBENZONE 0.03 g/1 g; OCTOCRYLENE 0.015 g/1 g
INACTIVE INGREDIENTS: CYCLOMETHICONE; EICOSYL POVIDONE (2 EICOSYL BRANCHES/REPEAT); DIMETHICONE; HYDROXYPROPYL CELLULOSE; ALCOHOL; ISOBUTYL STEARATE

Solbar Thirty 30SPF

Purpose

Sun screen.

OTC - ACTIVE INGREDIENT SECTION

Homosalate

Octinoxate

Oxybenzone

Avobenzone

Octocrylene

INACTIVE INGREDIENT SECTION

Alcohol

Isobutyl Stearate

Cyclomethicone

PVP/Eicosene Copolymer

Dimethicone

Klucel Hydroxypropylcellulose

Acrylates/Octylacrylamide Copolymer

Indications and Use

Helps prevent sunburn. If used as directed with other sun protection measures, decreases the risk of skin cancer and early skin aging caused by the sun.

Dosage and Administration:

Apply liberally and evenly to all sun exposed areas of DRY skin 15 minutes before sun exposure. Reapply after 80 minutes of swimming or sweating and immediately after towel drying. Apply at least every 2 hours. For children under 6 months, ask a physician.

Keep out of Reach of Children:

Yes. If swallowed, get medical help or contact a Poison Control Center right away.

Warnings

For external use only. Do not use on damaged or broken skin. Keep out of eyes. Rinse eyes thoroughly with water to remove. Stop use and ask a physician if rash or irritation develops and lasts. Store away from excessive heat and direct sun.